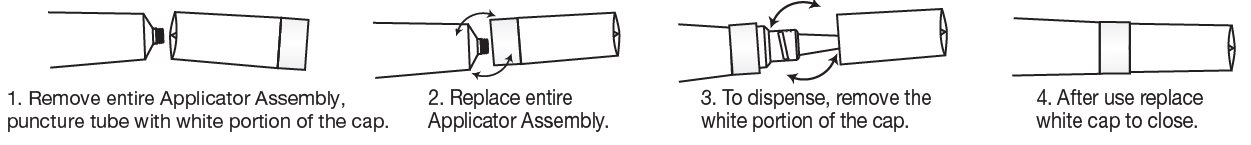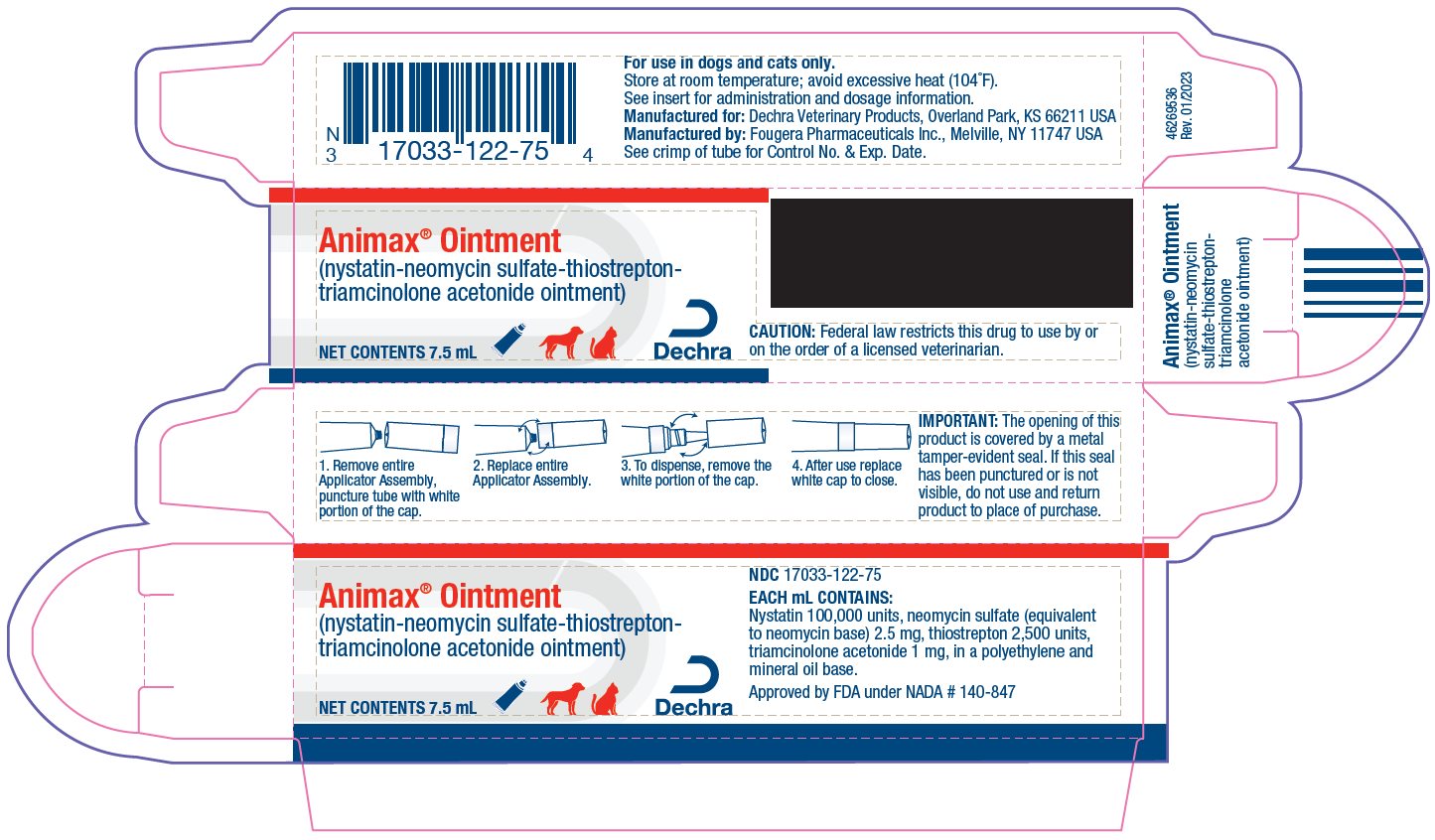 DRUG LABEL: Animax
NDC: 17033-122 | Form: OINTMENT
Manufacturer: Dechra Veterinary Products
Category: animal | Type: PRESCRIPTION ANIMAL DRUG LABEL
Date: 20230123

ACTIVE INGREDIENTS: NYSTATIN 100000 [USP'U]/1 mL; NEOMYCIN SULFATE 2.5 mg/1 mL; THIOSTREPTON 2500 [USP'U]/1 mL; TRIAMCINOLONE ACETONIDE 1 mg/1 mL
INACTIVE INGREDIENTS: HIGH DENSITY POLYETHYLENE; MINERAL OIL

Animax® Ointment
(nystatin-neomycin sulfate-thiostrepton-triamcinolone acetonide ointment)

VETERINARY

For use in dogs and cats only.

CAUTION: Federal law restricts this drug to use by or on the order of a licensed veterinarian.

DESCRIPTION:

Animax Ointment combines nystatin, neomycin sulfate, thiostrepton and triamcinolone acetonide in a non-irritating polyethylene and mineral oil base.

Each mL contains:
  nystatin 100,000 units
  neomycin sulfate equivalent to neomycin base 2.5 mg
  thiostrepton 2,500 units
  triamcinolone acetonide 1 mg
  The preparation is intended for local therapy in a variety of cutaneous disorders of dogs and cats; it is especially useful in disorders caused, complicated, or threatened by bacterial and/or candidal (monilial) infection.

ACTIONS:

By virtue of its four active ingredients, Animax Ointment provides four basic therapeutic effects: anti-inflammatory, antipruritic, antifungal and antibacterial. Triamcinolone acetonide is a potent synthetic corticosteroid providing rapid and prolonged symptomatic relief on topical administration. Inflammation, edema, and pruritus promptly subside, and lesions are permitted to heal. Nystatin is the first well-tolerated antifungal antibiotic of dependable efficacy for the treatment of cutaneous infections caused by Candida albicans (Monilia). Nystatin is fungistatic in vitro against a variety of yeast and yeast-like fungi including many fungi pathogenic to animals. No appreciable activity is exhibited against bacteria. Thiostrepton has a high order of activity against gram-positive organisms, including many which are resistant to other antibiotics; neomycin exerts antimicrobial action against a wide range of gram-positive and gram-negative bacteria. Together they provide comprehensive therapy against those organisms responsible for most superficial bacterial infections.

WARNINGS:

Clinical and experimental data have demonstrated that corticosteroids administered orally or by injection to animals may induce the first stage of parturition if used during the last trimester of pregnancy and may precipitate premature parturition followed by dystocia, fetal death, retained placenta, and metritis.

Additionally, corticosteroids administered to dogs, rabbits and rodents during pregnancy have resulted in cleft palate in the offspring. In dogs, other congenital anomalies have resulted: deformed forelegs, phocomelia, and anasarca.

Keep out of reach of children. If swallowed, get medical help or contact a Poison Control Center right away.

INDICATIONS:

Animax Ointment is particularly useful in the treatment of acute and chronic otitis of varied etiologies, in interdigital cysts in cats and dogs and in anal gland infections in dogs.

The preparation is also indicated in the management of dermatologic disorders characterized by inflammation and dry or exudative dermatitis, particularly those caused, complicated, or threatened by bacterial or candidal (Candida albicans) infections. It is also of value in eczematous dermatitis, contact dermatitis, and seborrheic dermatitis; and as an adjunct in the treatment of dermatitis due to parasitic infestation.

PRECAUTIONS:

Animax Ointment is not intended for the treatment of deep abscesses or deep-seated infections such as inflammation of the lymphatic vessels. Parenteral antibiotic therapy is indicated in these infections.

Animax Ointment has been extremely well tolerated. Cutaneous reactions attributable to its use have been extremely rare. The occurrence of systemic reactions is rarely a problem with topical administration. There is some evidence that corticosteroids can be absorbed after topical application and cause systemic effects. Therefore, an animal receiving Animax Ointment therapy should be observed closely for signs such as polydipsia, polyuria, and increased weight gain.

Animax Ointment is not generally recommended for the treatment of deep or puncture wounds or serious burns.

Sensitivity to neomycin may occur. If redness, irritation, or swelling persists or increases, discontinue use. Do not use if pus is present since the drug may allow the infection to spread.

Avoid ingestion. Oral or parenteral use of corticosteroids (depending on dose, duration of use, and specific steroid) may result in inhibition of endogenous steroid production following drug withdrawal.

SIDE EFFECTS:

SAP and SGPT (ALT) enzyme elevations, polydipsia and polyuria, vomiting, and diarrhea (occasionally bloody) have been observed following parenteral or systemic use of synthetic corticosteroids in dogs.

Cushing's syndrome has been reported in association with prolonged or repeated steroid therapy in dogs. Temporary hearing loss has been reported in conjunction with treatment of otitis with products containing corticosteroids. However, regression usually occurred following withdrawal of the drug. Hearing loss, with varying degrees of recovery, has been reported with the use of Animax Ointment. If hearing dysfunction is noted during the course of treatment with Animax Ointment, discontinue its use.

To report suspected adverse drug events, for technical assistance or to obtain a copy of the safety data sheet (SDS), contact Dechra at (866) 933-2472.

For additional information about adverse drug experience reporting for animal drugs, contact FDA at 1-888-FDA-VETS or online at http://www.fda.gov/reportanimalae.

CAUTION:

Before instilling any medication into the ear, examine the external ear canal thoroughly to be certain the tympanic membrane is not ruptured in order to avoid the possibility of transmitting infection to the middle ear as well as damaging the cochlea or vestibular apparatus from prolonged contact. If hearing or vestibular dysfunction is noted during the course of treatment, discontinue the use of Animax Ointment.

DOSAGE AND ADMINISTRATION:

Frequency of administration is dependent on the severity of the condition. For mild inflammations, application may range from once daily to once a week; for severe conditions Animax Ointment may be applied as often as two to three times daily, if necessary.
Frequency of treatment may be decreased as improvement occurs.
Wear gloves during the administration of the ointment or wash hands immediately after application.

Otitis

Clean ear canal of impacted cerumen. Inspect canal and remove any foreign bodies such as grass awns, ticks, etc. Instill three to five drops of Animax Ointment.
Preliminary use of a local anesthetic may be advisable.

Infected Anal Glands, Cystic Areas, etc.

Drain gland or cyst and then fill with Animax Ointment.

Other Dermatologic Disorders

Clean affected areas, removing any encrusted discharge or exudate. Apply Animax Ointment sparingly in a thin film.

HOW SUPPLIED:

Animax Ointment is supplied in tubes as follows:

7.5 mL tubes NDC 17033-122-75
15 mL tubes NDC 17033-122-15
30 mL tubes NDC 17033-122-30

STORAGE: Store at room temperature; avoid excessive heat (104°F).

TO OPEN:

Use cap to puncture seal.

IMPORTANT:

The opening of this product is covered by a metal tamper-evident seal.

If this seal has been punctured or is not visible, do not use and return product to place of purchase.

Approved by FDA under NADA # 140-847

MANUFACTURED FOR:
Dechra Veterinary Products

Overland Park, KS 66211 USA

MANUFACTURED BY:
Fougera Pharmaceuticals Inc.

Melville, NY 11747 USA

46269508 Rev. 01/2023

PRINCIPAL DISPLAY PANEL - 7.5 mL Carton

Animax® Ointment
(nystatin-neomycin sulfate-thiostrepton-triamcinolone acetonide ointment)
NET CONTENTS 7.5 mL
NDC 17033-122-75